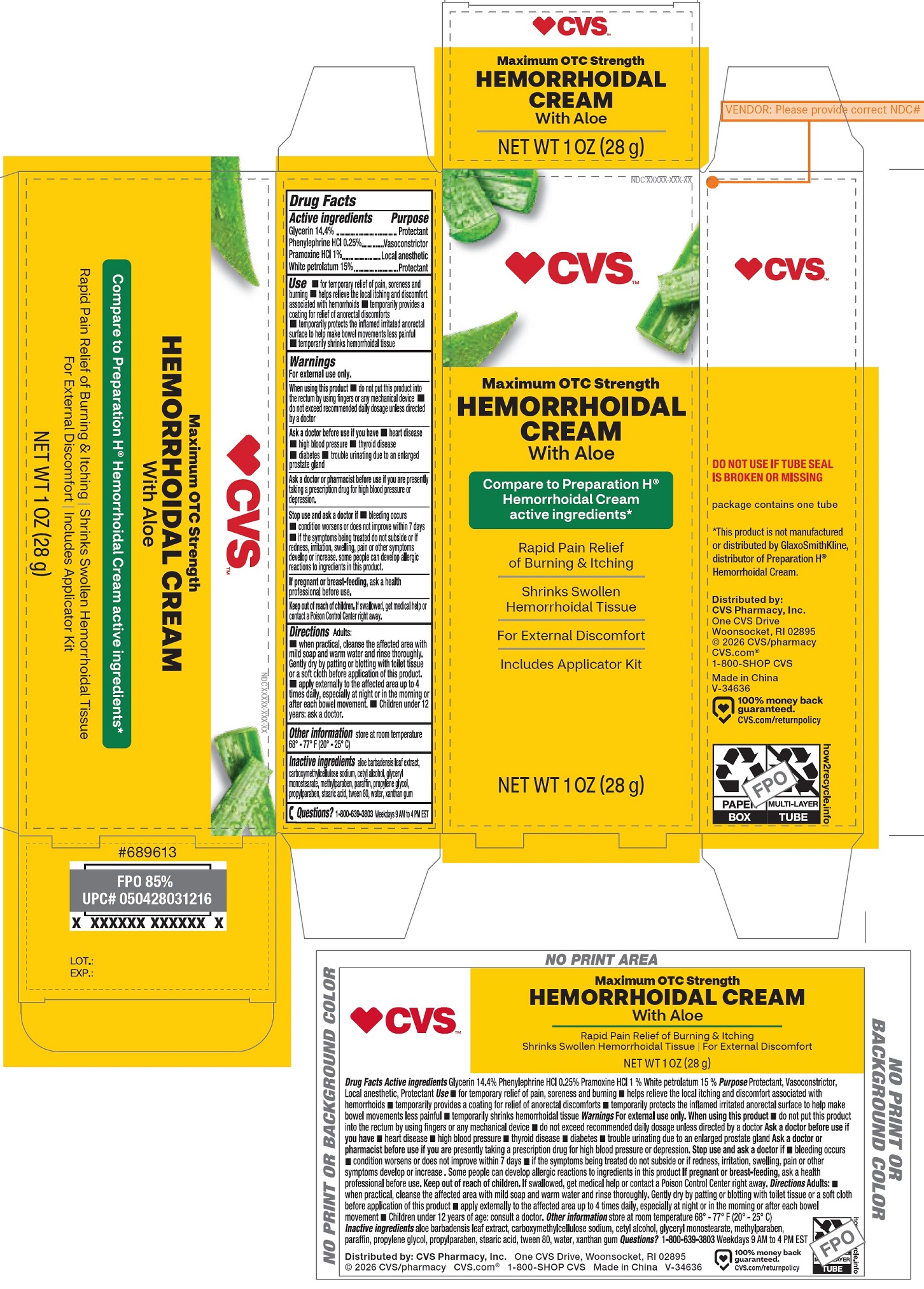 DRUG LABEL: CVS Maximum OTC Strength Hemorrhoidal with Aloe
NDC: 51316-203 | Form: CREAM
Manufacturer: CVS PHARMACY,INC
Category: otc | Type: HUMAN OTC DRUG LABEL
Date: 20260102

ACTIVE INGREDIENTS: GLYCERIN 144 mg/1 g; PHENYLEPHRINE HYDROCHLORIDE 2.5 mg/1 g; PRAMOXINE HYDROCHLORIDE 10 mg/1 g; WHITE PETROLATUM 150 mg/1 g
INACTIVE INGREDIENTS: ALOE VERA LEAF; CARBOXYMETHYLCELLULOSE SODIUM, UNSPECIFIED; CETYL ALCOHOL; GLYCERYL MONOSTEARATE; METHYLPARABEN; PARAFFIN; PROPYLENE GLYCOL; PROPYLPARABEN; STEARIC ACID; POLYSORBATE 80; WATER; XANTHAN GUM

CVS Maximum OTC Strength Hemorrhoidal Cream with Aloe

Active ingredients

Glycerin 14.4%
Phenylephrine HCl 0.25%
Pramoxine HCl 1%
White petrolatum 15%

Purpose

Protectant
Vasoconstrictor
Local anesthetic
Protectant

Use

- for temporary relief of pain, soreness and burning
- helps relieve the local itching and discomfort associated with hemorrhoids
- temporarily provides a coating for relief of anorectal discomforts
- temporarily protects the inflamed irritated anorectal surface to help make bowel movements less painful
- temporarily shrinks hemorrhoidal tissue

Warnings

For external use only.

When using this product

- do not put this product into the rectum by using fingers or any mechanical device
- do not exceed recommended daily dosage unless directed by a doctor

Ask a doctor before use if you have

- heart disease
- high blood pressure
- thyroid disease
- diabetes
- trouble urinating due to an enlarged prostate gland

Ask a doctor or pharmacist before use if you are

presently taking a prescription drug for high blood pressure or depression

Stop use and ask a doctor if

- bleeding occurs
- condition worsens or does not improve within 7 days
- if the symptoms being treated do not subside or if redness, irritation, swelling, pain or other symptoms develop or increase. some people can develop allergic reactions to ingredients in this product.

If pregnant or breast-feeding,

ask a health professional before use.

Keep out of reach of children.

If swallowed, get medical help or contact a Poison Control Center right away.

Directions

Adults:

- when practical, cleanse the affected area with mild soap and warm water and rinse thoroughly. Gently dry by patting or blotting with toilet tissue or a soft cloth before application of this product.
- apply externally to the affected area up to 4 times daily, especially at night or in the morning or after each bowel movement.
- Children under 12 years: ask a doctor.

Other information

store at room temperature 68°-77°F (20°-25°C)

Inactive ingredients

aloe barbadensis leaf extract, carboxymethylcellulose sodium, cetyl alcohol, glyceryl monostearate, methylparaben, paraffin, propylene glycol, propylparaben, stearic acid, tween 80, water, xanthan gum

Questions?

1-800-639-3803Weekdays 9 AM to 4 PM EST